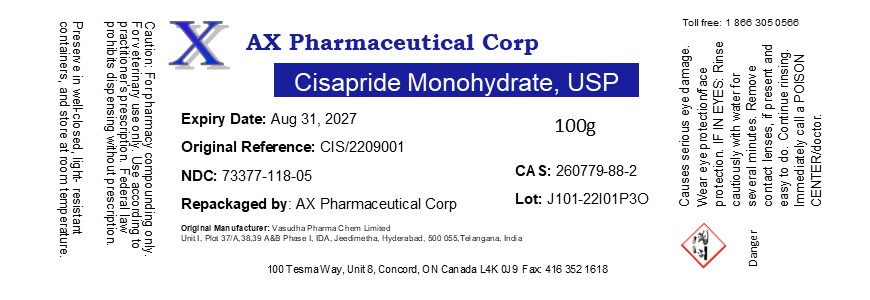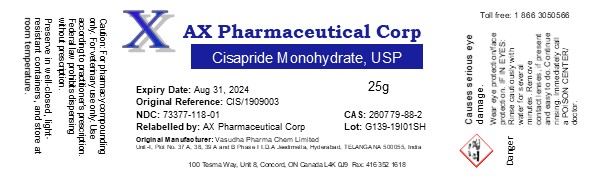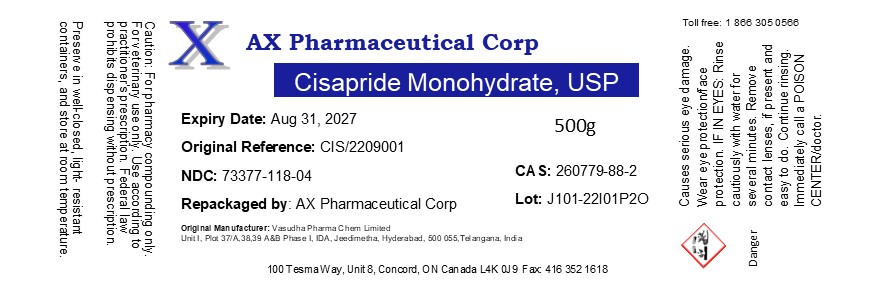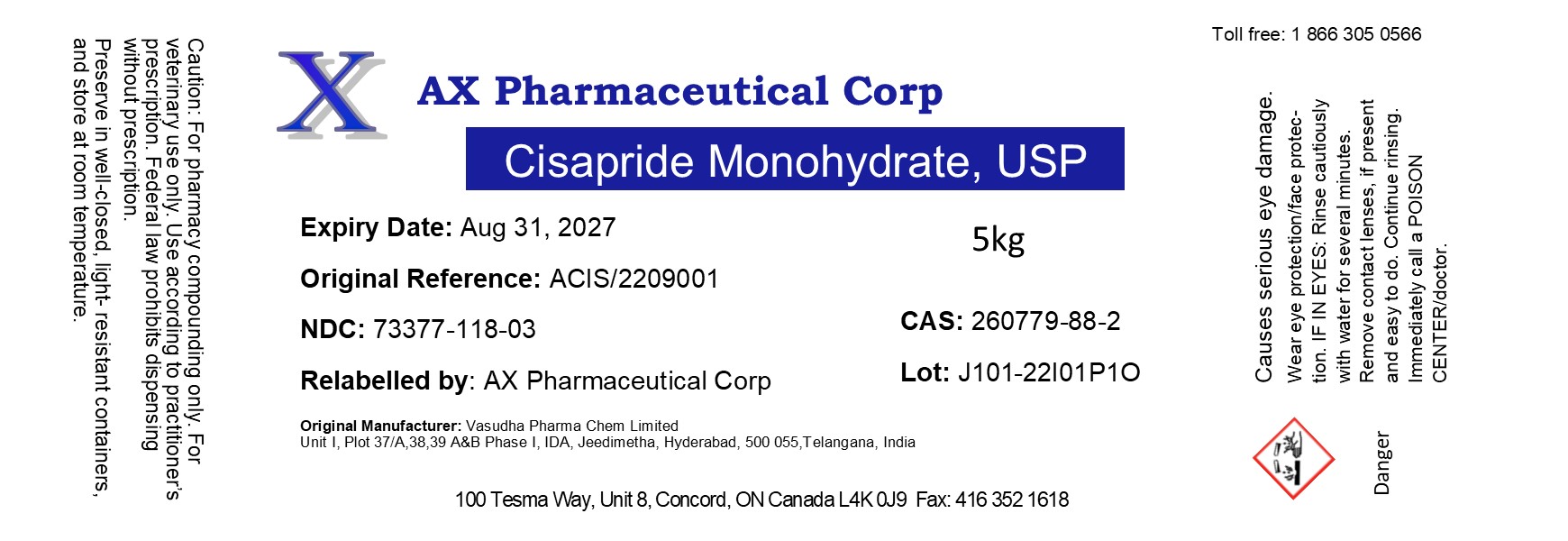 DRUG LABEL: Cisapride Monohydrate
NDC: 73377-118 | Form: POWDER
Manufacturer: AX Pharmaceutical Corp
Category: other | Type: BULK INGREDIENT - ANIMAL DRUG
Date: 20251103

ACTIVE INGREDIENTS: CISAPRIDE MONOHYDRATE 1 g/1 g

Cisapride Monohydrate